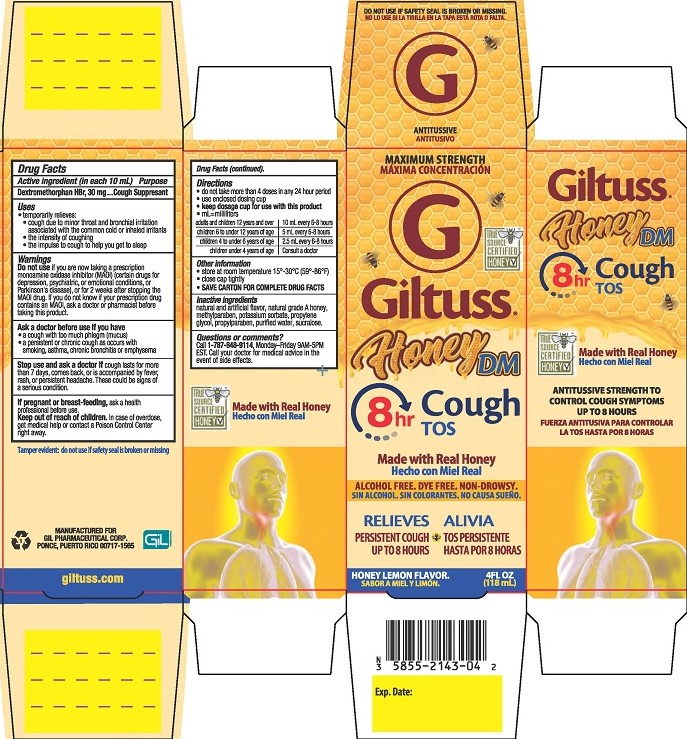 DRUG LABEL: Giltuss Honey DM Cough
NDC: 58552-143 | Form: SOLUTION
Manufacturer: Gil Pharmaceutical Corp
Category: otc | Type: HUMAN OTC DRUG LABEL
Date: 20251009

ACTIVE INGREDIENTS: DEXTROMETHORPHAN HYDROBROMIDE 30 mg/10 mL
INACTIVE INGREDIENTS: POTASSIUM SORBATE; WATER; PROPYLENE GLYCOL; SUCRALOSE; HONEY; METHYLPARABEN; PROPYLPARABEN

Giltuss Honey DM

Drug Facts

Active ingredient (in each 10 mL)

Dextromethorphan HBr, 30 mg

Purposes

Cough Suppresant

Uses

- temporarily relieves:
- cough due to minor throat and bronchial irritation associated with the common cold or inhaled irritants
- the intensity of coughing
- the impulse to cough to help your child get to sleep

Warnings

DO NOT USE

Do not useif you are now taking a prescription monoamine oxidase inhibitor (MAOI) (certain drugs for depression, psychiatric, or emotional conditions, or Parkinson’s disease), or for 2 weeks after stopping the MAOI drug. If you do not know if your prescription drug contains an MAOI, ask a doctor or pharmacist before taking this product.

Ask a doctor before use if you have

- a cough with too much phlegm (mucus)
- a persistent or chronic cough as occurs with smoking, asthma, chronic bronchitis, or emphysema

Stop use and ask a doctor ifcough lasts for more than 7 days, comes back, or is accompanied by fever, rash or persistent headache. These could be signs of a serious condition.

PREGNANCY OR BREAST FEEDING

If pregnant or breast-feeding, ask a health professional before use.

Keep out of reach of children.In case of overdose, get medical help or contact a Poison Control Center right away.

Directions

- do not take more than 4 doses in any 24-hour period
- use enclosed dosing cup
- keep dosage cup for use with this product
- ml = milliliters
  adults and children 12 years and over | 10 mL every 6-8 hours
  children 6 to under 12 years of age | 5 mL every 6-8 hours
  children 4 to under 6 years of age | 2.5 mL every 6-8 hours
  children under 4 years of age | Consult a doctor

Other information

- store at room temperature 15°-30°C (59°-86°F)
- close cap tightly
- SAVE CARTON FOR COMPLETE DRUG FACTS

INACTIVE INGREDIENT

Inactive ingredientsnatural and artificial flavor, natural grade A honey, methylparaben, potassium sorbate, propylene glycol, propylparaben, purified water, sucralose.

Questions or comments?Call 1-787-848-9114, Monday-Friday 9AM - 5PM EST. Call your doctor for medical advice in the event of side effects.

Tamper Evident: do not use if safety seal is broken or missing.

MANUFACTURED FOR

GIL PHARMACEUTICAL CORP.

PONCE, PUERTO RICO 00717-1565

giltuss.com

PACKAGE LABEL

MAXIMUM STRENGTH

Giltuss®

Honey DM Cough

Made with real honey

ALCOHOL FREE. DYE FREE. NON-DROWSY

RELIEVES

PERSISTENT COUGH UP TO 8 HOURS

HONEY LEMON FLAVOR.

4FL OZ (118 mL)